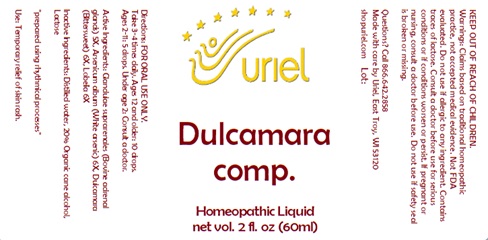 DRUG LABEL: Dulcamara comp.
NDC: 48951-4010 | Form: LIQUID
Manufacturer: Uriel Pharmacy Inc.
Category: homeopathic | Type: HUMAN OTC DRUG LABEL
Date: 20240709

ACTIVE INGREDIENTS: BOS TAURUS ADRENAL GLAND 5 [hp_X]/1 mL; ARSENIC TRIOXIDE 6 [hp_X]/1 mL; SOLANUM DULCAMARA TOP 6 [hp_X]/1 mL; LOBELIA SPICATA LEAF 6 [hp_X]/1 mL
INACTIVE INGREDIENTS: WATER; SODIUM CHLORIDE; LACTOSE, UNSPECIFIED FORM

Dulcamara comp.

INDICATIONS AND USAGE

Directions: FOR ORAL USE ONLY.

DOSAGE AND ADMINISTRATION

Take 3-4 times daily. Ages 12 and older: 10 drops. Ages 2-11: 5 drops. Under age 2: Consult a doctor.

ACTIVE INGREDIENT

Active Ingredients: Glandulae suprarenales (Bovine adrenal glands) 5X, Arsenicum album (White arsenic) 6X, Dulcamara (Bittersweet) 6X, Lobelia 6X

Inactive Ingredients: Distilled water, Organic cane alcohol, Lactose

PURPOSE

Use: Temporary relief of skin rash.

KEEP OUT OF REACH OF CHILDREN.

WARNINGS

Warnings: Claims based on traditional homeopathic practice, not accepted medical evidence. Not FDA evaluated. Do not use if allergic to any ingredient. Contains traces of lactose. Consult a doctor before use for serious conditions or if conditions worsen or persist. If pregnant or nursing, consult a doctor before use. Do not use if safety seal is broken or missing.

QUESTIONS

Questions? Call 866.642.2858 Made with care by Uriel, East Troy, WI 53120 shopuriel.com Lot: